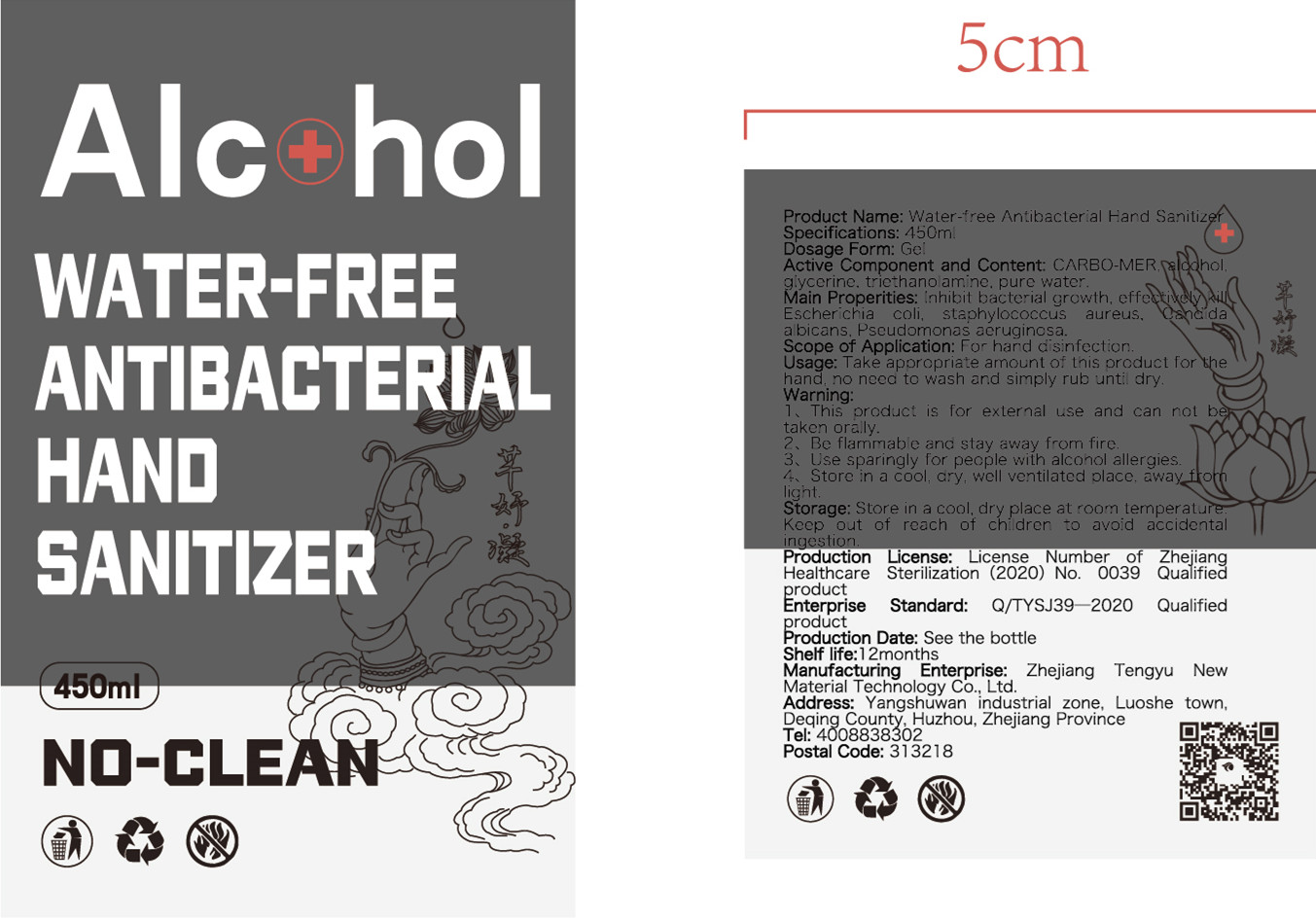 DRUG LABEL: Water-free Antibacterial  Hand Sanitizer
NDC: 54983-002 | Form: GEL
Manufacturer: Zhejiang Tengyu New Material Technology Co., Ltd.
Category: otc | Type: HUMAN OTC DRUG LABEL
Date: 20200411

ACTIVE INGREDIENTS: ALCOHOL 270 mL/450 mL
INACTIVE INGREDIENTS: METHYLTRIETHANOLAMMONIUM METHOSULFATE; GLYCERIN; CARBOMER HOMOPOLYMER, UNSPECIFIED TYPE; WATER; METHYL BENZOATE

DOSAGE AND ADMINISTRATION

Store in a cool. ary, well ventilated place. away from light.

INACTIVE INGREDIENT

Carbo-mer

Pure Water

Ethyl alcohol

Essence

Gycerinum

Corrosion remover

Triethanolamine

INDICATIONS AND USAGE

Take appropriate amount of this product for the hand. no need to wash an.d simply rub until dry.

ACTIVE INGREDIENT

Ethyl alcohol

keep out of children

PURPOSE

Disinfection
Sterilization
No Rinseing

WARNINGS

1、This product is for external use and can not be taken oraly.
2、Be flammable and stay away from fire.
3、Use sparingly for people with alcohol allergies.
4、Store in a cool dry, well ventilated place. away from light.